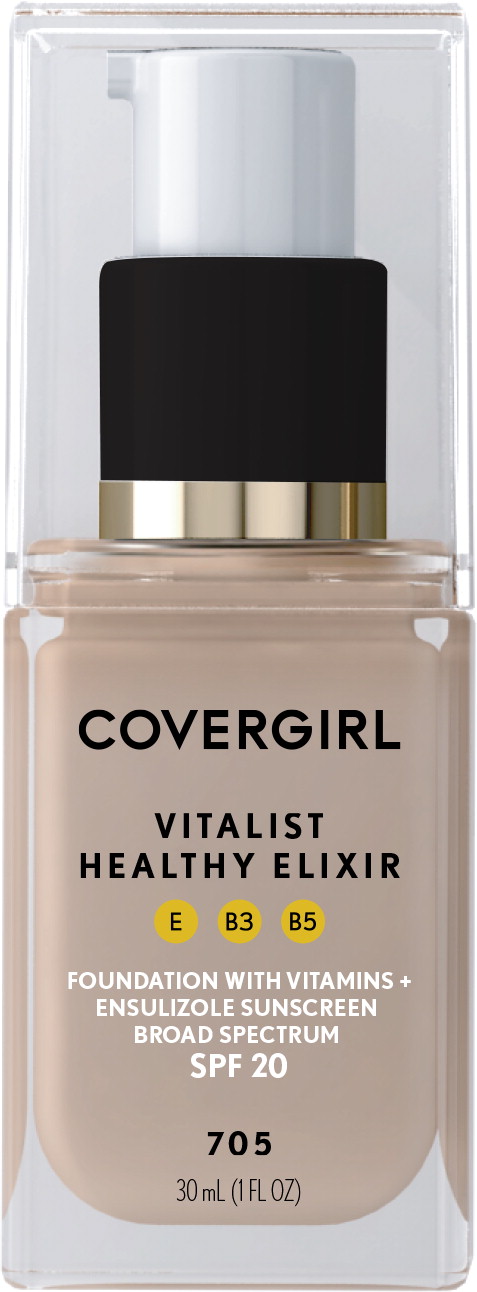 DRUG LABEL: Covergirl Vitalist Healthy Foundation with Vitamins plus Ensulizole Sunscreen Broad Spectrum SPF 20 (All shades)

NDC: 22700-200 | Form: LIQUID
Manufacturer: Noxell Corporation
Category: otc | Type: HUMAN OTC DRUG LABEL
Date: 20230128

ACTIVE INGREDIENTS: ENSULIZOLE
 3 g/100 mL
INACTIVE INGREDIENTS: WATER; CYCLOMETHICONE 5; PROPYLENE GLYCOL; GLYCERIN; TITANIUM DIOXIDE; DIMETHICONE; TALC; ALUMINUM STARCH OCTENYLSUCCINATE; PEG/PPG-18/18 DIMETHICONE; SODIUM CHLORIDE; PHENOXYETHANOL; SODIUM HYDROXIDE; TRIHYDROXYSTEARIN; ARACHIDYL BEHENATE; CAPRYLYL GLYCOL; 1,2-HEXANEDIOL; METHICONE (20 CST); SODIUM BENZOATE; SILICON DIOXIDE; POLYGLYCERYL-4 ISOSTEARATE; HEXYL LAURATE; .ALPHA.-TOCOPHEROL ACETATE; PANTHENOL; NIACINAMIDE; ETHYLENE BRASSYLATE; BEHENIC ACID; HIGH DENSITY POLYETHYLENE; ISOPROPYL TITANIUM TRIISOSTEARATE; FERRIC OXIDE RED

Drug Facts

Active ingredient

Ensulizole 3%.

Purpose

Sunscreen

Uses

- helps prevent sunburn
- if used as directed with other sun protection measures (see Directions), decreases the risk of skin cancer and early skin aging caused by the sun

Warnings

- For external use only

- Do not use on damaged or broken skin

- When using this product keep out of eyes. Rinse with water to remove

- Stop use and ask a doctor if rash occurs

- Keep out of reach of children.

If product is swallowed, get medical help or contact a Poison Control Center right away

Directions

- apply liberally 15 minutes before sun exposure
- reapply at least every 2 hours
- use water resistant sunscreen if swimming or sweating
- Sun Protection

Measures: Spending time in the sun increases your risk of skin cancer and early skin aging. To decrease this risk, regularly use a sunscreen with a Broad Spectrum SPF value of 15 or higher and other sun protection measures including:

- limit time in sun, especially from 10 a.m. – 2 p.m.
- wear long-sleeved shirts, pants, hats, and sunglasses
- children under 6 months: ask a doctor

Other information

- protect this product from excessive heat and direct sun

Inactive ingredients

Water, cyclopentasiloxane, propylene glycol, glycerin, titanium dioxide, dimethicone, talc, aluminum starch octenylsuccinate, peg/ppg-18/18 dimethicone, pvp, sodium chloride, phenoxyethanol, sodium hydroxide, trihydroxystearin, arachidyl behenate, caprylyl glycol, 1,2-hexanediol, methicone, fragrance, sodium benzoate, silica, acrylonitrile/methyl methacrylate/vinylidene chloride copolymer, synthetic wax, polyglyceryl-4 isostearate, hexyl laurate, cetyl peg/ppg-10/1 dimethicone, tocopheryl acetate, panthenol, niacinamide, ethylene brassylate, behenic acid, polyethylene, isopropyl titanium triisostearate, iron oxides

Questions?

Call 1-800-426-8374

MADE IN USAOF US & IMPORTED PARTS

COTYUS LLC, NEW YORK, NY 10118

Principal Display Panel - Covergirl Vitalist Healthy Elixir Label

COVERGIRL

vitalist

HEALTHY

ELIXIR

FOUNDATION WITH VITAMINS +
ENSULIZOLE SUNSCREEN
BROAD SPECTRUM SPF 20

705

30 mL (1 FL OZ)